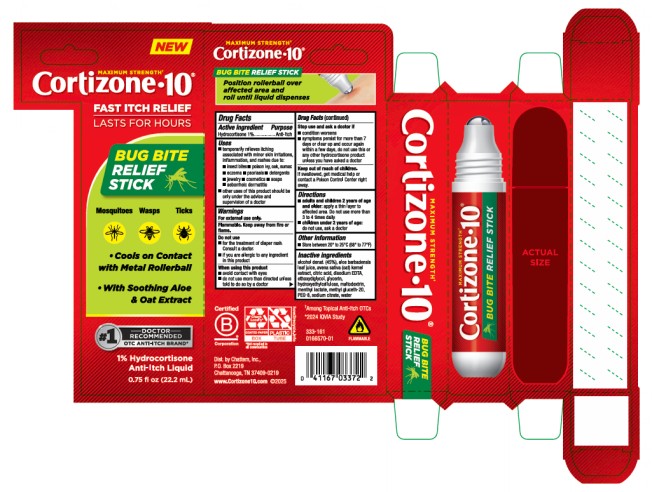 DRUG LABEL: Cortizone 10 Bug Bite Relief
NDC: 41167-0337 | Form: LIQUID
Manufacturer: Chattem, Inc.
Category: otc | Type: HUMAN OTC DRUG LABEL
Date: 20260115

ACTIVE INGREDIENTS: HYDROCORTISONE 0.2 g/22.2 mL
INACTIVE INGREDIENTS: ALCOHOL; ALOE BARBADENSIS LEAF JUICE; OAT; CITRIC ACID; EDETATE DISODIUM; ETHOXYDIGLYCOL; GLYCERIN; HYDROXYETHYLCELLULOSE; MALTODEXTRIN; MENTHYL LACTATE; METHYL GLUCETH-20; PEG-8; SODIUM CITRATE; WATER

Cortizone-10 Bug Bite Relief Stick

Cortizone 10 Bug Bite Relief Stick

Drug Facts

Purpose

Hydrocortisone 1%.........................................................................................................................Anti-Itch

Uses

■ temporarily relieves itching associated with minor skin irritations, inflammation, and rashes due to:

■ insect bites ■ poison ivy, oak, sumac ■ eczema ■ psoriasis ■ detergents ■ jewelry ■ cosmetics

■ soaps ■ seborrheic dermatitis

■ other uses of this product should be only under the advice and supervision of a doctor

Warnings

For external use only.

Flammable. Keep away from fire or flame.

Do not use

■ for the treatment of diaper rash. Consult a doctor.

■ if you are allergic to any ingredient in this product

When using this product

■ avoid contact with eyes ■ do not use more than directed unless told to do so by a doctor

Stop use and ask a doctor if

■ condition worsens

■ symptoms persist for more than 7 days or clear up and occur again within a few days, do not use this or any other hydrocortisone product unless you have asked a doctor

Keep out of reach of children.

If swallowed, get medical help or contact a Poison Control Center right away.

Directions

■ adults and children 2 years of age and older: apply a thin layer to affected area. Do not use more than 3 to 4 times daily.

■ children under 2 years of age: do not use, ask a doctor

Other Information

■ Store between 20° to 25°C (68° to 77°F)

Inactive ingredients

alcohol denat. (45%), aloe barbadensis leaf juice, avena sativa (oat) kernel extract, citric acid, disodium EDTA, ethoxydiglycol, glycerin, hydroxyethylcellulose, maltodextrin, menthyl lactate, methyl gluceth-20, PEG-8, sodium citrate, water

Keep carton as it contains important information.

PRINCIPAL DISPLAY PANEL

Cortizone 10
Bug Bite Relief Stick
0.75 fl oz (22.2 mL)